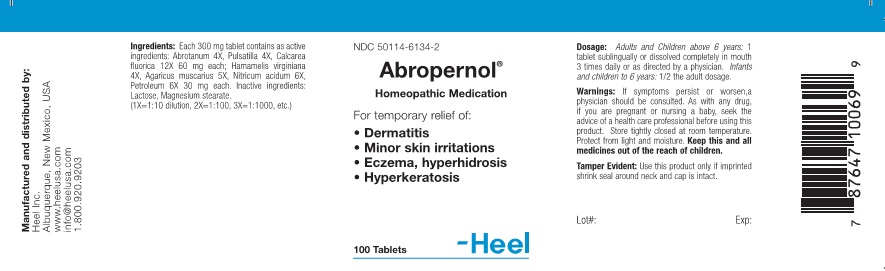 DRUG LABEL: Abropernol
NDC: 50114-6134 | Form: TABLET
Manufacturer: Heel Inc
Category: homeopathic | Type: HUMAN OTC DRUG LABEL
Date: 20111212

ACTIVE INGREDIENTS: ARTEMISIA ABROTANUM FLOWERING TOP 4 [hp_X]/300 mg; PULSATILLA VULGARIS 4 [hp_X]/300 mg; CALCIUM FLUORIDE 12 [hp_X]/300 mg; HAMAMELIS VIRGINIANA ROOT BARK/STEM BARK 4 [hp_X]/300 mg; AMANITA MUSCARIA VAR. MUSCARIA FRUITING BODY 5 [hp_X]/300 mg; NITRIC ACID 6 [hp_X]/300 mg; KEROSENE 6 [hp_X]/300 mg
INACTIVE INGREDIENTS: LACTOSE; MAGNESIUM STEARATE

Abropernol Tablet

KEEP OUT OF REACH OF CHILDREN

Keep this and all medications out of the reach of children.

INDICATIONS AND USAGE

For the temporary relief of:

- Dermatitus
- Minor skin irritations
- Eczema, hyperhidrosis
- Hyperkeratosis

WARNINGS

If symptoms persist or worsen, a physician should be consulted. As with any drug, if you are pregnant or nursing a baby, seek the advise of a health care professional before using this product.

DOSAGE AND ADMINISTRATION

Adults and children above 6 years: 1 tablet sublingually or dissolved completely in mouth 3 times daily or as directed by a physician.
Infants and children to 6 years: 1/2 the adult dosage.

ACTIVE INGREDIENT

Each 300mg tablet contains as active ingredients: Abrotanum 4X, Pulsatilla 4X, Calcarea fluorica 12X 60 mg each; Hamamelis virginiana 4X, Agaricus muscarius 5X, Nitricum acidum 6X, Petroleum 6X 30 mg each.

INACTIVE INGREDIENT

Inactive ingredients: Lactose, Magnesium Stearate

PURPOSE

Dermatitus, Minor skin irritations, Eczema, hyperhidrosis, Hyperkeratosis